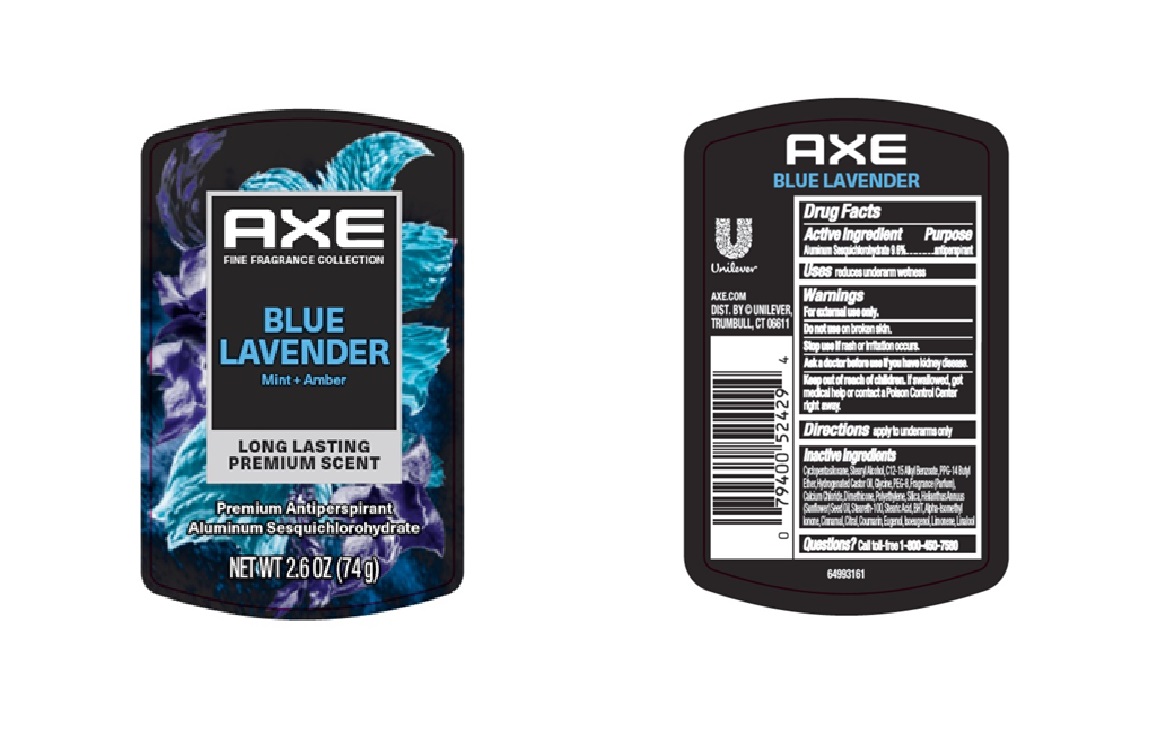 DRUG LABEL: Axe
NDC: 64942-2378 | Form: STICK
Manufacturer: Conopco d/b/a Unilever
Category: otc | Type: HUMAN OTC DRUG LABEL
Date: 20250718

ACTIVE INGREDIENTS: ALUMINUM SESQUICHLOROHYDRATE 9.6 g/100 g
INACTIVE INGREDIENTS: CYCLOPENTASILOXANE; STEARETH-100; STEARIC ACID; COUMARIN; EUGENOL; PPG-14 BUTYL ETHER; PEG-8; HYDROGENATED CASTOR OIL; CITRAL; ISOEUGENOL; LINALOOL; C12-15 ALKYL BENZOATE; ALPHA-ISOMETHYL IONONE; POLYETHYLENE; HELIANTHUS ANNUUS (SUNFLOWER) SEED OIL; CINNAMAL; STEARYL ALCOHOL; CALCIUM CHLORIDE; LIMONENE, (+)-; SILICA; BHT; GLYCINE; DIMETHICONE

Axe Blue Lavender Mint and Amber Long Lasting Premium Scent Premium Antiperspirant

DESCRIPTION

Axe Blue Lavender Mint and Amber Long Lasting Premium Scent Premium Antiperspirant

ACTIVE INGREDIENT

Aluminum Sesquichlorohydrate 9.6%

PURPOSE

Antiperspirant

INDICATIONS AND USAGE

apply to underarms only

WARNINGS

For external use only.
• Do not use on broken skin.• Ask a doctor before
use if you have kidney disease. • Stop use if rash or irritation occurs.

Keep out of reach of children. If swallowed,get medical help or contact a Poison Control Center right away

DOSAGE AND ADMINISTRATION

apply to underarms only

INACTIVE INGREDIENT

Cyclopentasiloxane,Stearyl Alcohol,C12-15 Alkyl Benzoate,PPG-14 Butyl Ether,Hydrogenated Castor Oil,Glycine,PEG-8,Fragrance (Parfum), Calcium Chloride,Dimethicone,Polyethylene,Silica,Helianthus Annuus (Sunflower) Seed Oil,Steareth-100,Stearic Acid,BHT,Alpha-Isomethyl Ionone,Cinnamal,Citral,Coumarin,Eugenol,Isoeugenol,Limonene,Linalool

QUESTIONS

call 1-800-761-3683